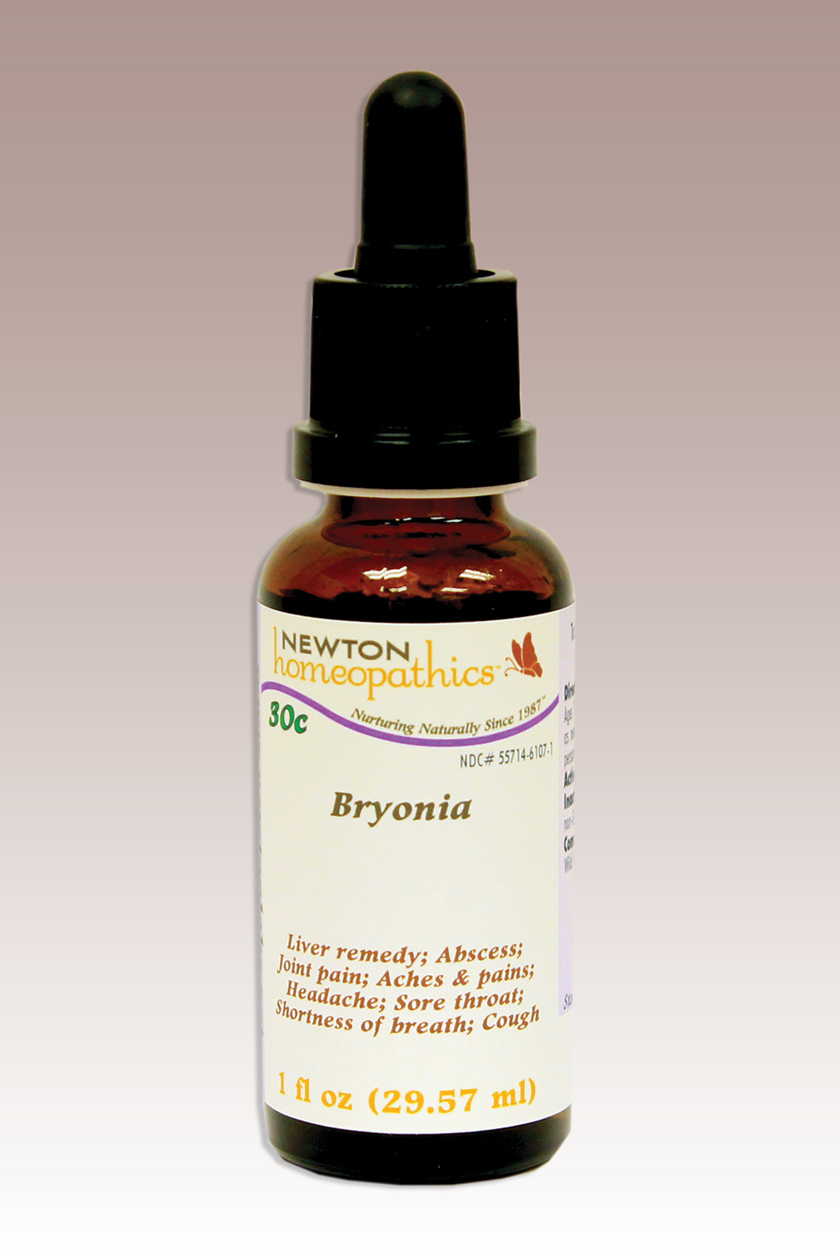 DRUG LABEL: Bryonia 
NDC: 55714-6107 | Form: LIQUID
Manufacturer: Newton Laboratories, Inc.
Category: homeopathic | Type: HUMAN OTC DRUG LABEL
Date: 20110901

ACTIVE INGREDIENTS: Bryonia Alba Root 15 [hp_X]/1 mL
INACTIVE INGREDIENTS: Alcohol; Water

Bryonia

INDICATIONS & USAGE SECTION

Liver Remedy, Abscess, Joint Pain, Aches & Pains, Headache, Sore Throat, Shortness of Breath, Cough.

DOSAGE & ADMINISTRATION SECTION

Directions: Ages 12 and up, take 6 drops by mouth (ages 0 to 11, give 3 drops) as needed or as directed by a health professional. Sensitive persons begin with 1 drop and gradually increase to full dose.

OTC - ACTIVE INGREDIENT SECTION

Bryonia 15x, 10x, 200c, 30c.

PURPOSE SECTION

Liver Remedy, Abscess, Joint Pain, Aches & Pains, Headache, Sore Throat, Shortness of Breath, Cough.

INACTIVE INGREDIENT SECTION

Inactive Ingredients: USP Purified Water; USP Gluten-free, non-GMO, organic cane alcohol 20%.

OTC - QUESTIONS SECTION

www.newtonlabs.net Newton Laboratories, Inc. FDA Est # 1051203 - Conyers, GA 30012
Questions? 1.800.448.7256

WARNINGS SECTION

Warning: Keep out of reach of children. Do not use if tamper-evident seal is broken or missing. If symptoms worsen or persist for more than a few days, consult a doctor. If pregnant or breast-feeding, ask a doctor before use.

OTC - PREGNANCY OR BREAST FEEDING SECTION

Consult a licensed healthcare professional if pregnant, nursing or if symptoms worsen or persist for more than a few days.

OTC - KEEP OUT OF REACH OF CHILDREN SECTION

Keep out of reach of children.